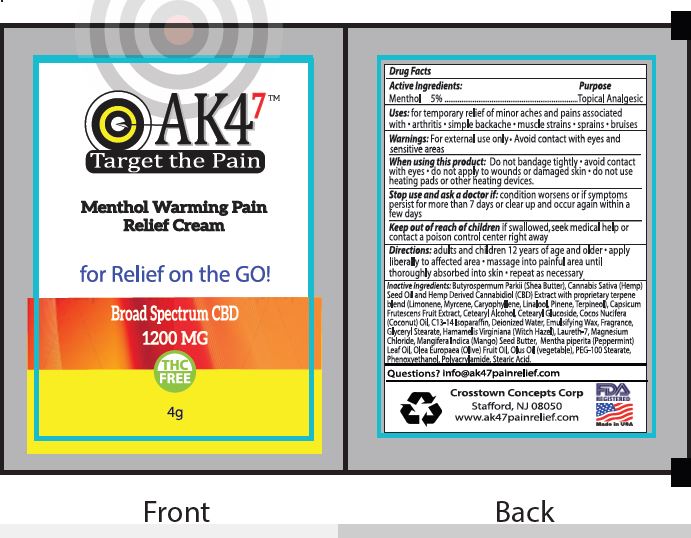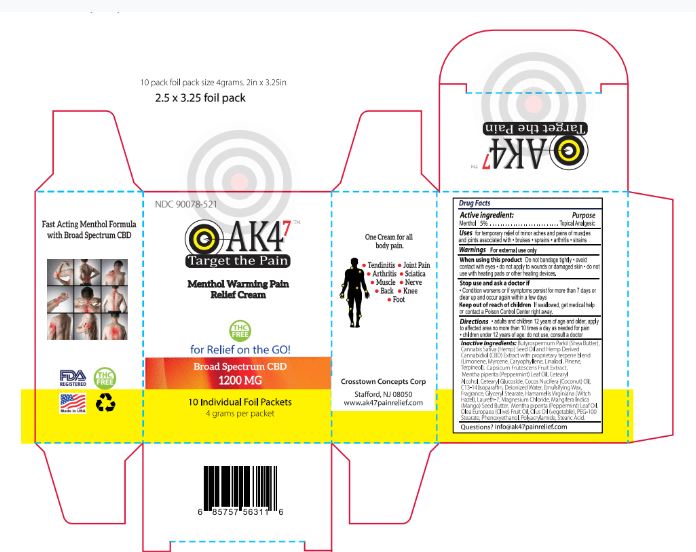 DRUG LABEL: AK47 Menthol Warming
NDC: 76348-575 | Form: CREAM
Manufacturer: RENU LABORATORIES, INC.
Category: otc | Type: HUMAN OTC DRUG LABEL
Date: 20200813

ACTIVE INGREDIENTS: MENTHOL 0.2 g/4 g
INACTIVE INGREDIENTS: OLIVE OIL; CORN OIL; POLYACRYLAMIDE (10000 MW); LINALOOL, (+/-)-; TABASCO PEPPER; CETOSTEARYL ALCOHOL; CETEARYL GLUCOSIDE; C13-14 ISOPARAFFIN; CARYOPHYLLENE; PINENE; TERPINEOL; COCONUT OIL; PEG-100 STEARATE; PHENOXYETHANOL; MYRCENE; WATER; WHITE WAX; WITCH HAZEL; MANGIFERA INDICA SEED BUTTER; PEPPERMINT OIL; CANNABIDIOL; SHEA BUTTER; CANNABIS SATIVA SEED OIL; LIMONENE, (+)-; GLYCERYL MONOSTEARATE; LAURETH-7; MAGNESIUM CHLORIDE; STEARIC ACID

AK4^7 Menthol Warming Cream

Active Ingredients

Menthol 5 percent

Purpose

Topical Analgesic

INDICATIONS AND USAGE

Uses: for temporary relief of minor aches and pains associated with

- arthritis
- simple backache
- muscle strains
- sprains
- bruises

When using this product: Do not bandage tightly • avoid contact with eyes • do not apply to wounds or damaged skin • do not use heating pads or other heating devices.

Warnings

For external use only

Avoid contact with eyes and sensitive areas

Stop use and ask a doctor if:

condition worsens or if symptoms persist for more than 7 days or clear up and occur again within a few days

Keep out of reach of children

If swallowed, seek medical help or contact a poison control center right away

Directions

adults and children 12 years of age and older

- apply liberally to affected area
- massage into painful area until thoroughly absorbed into skin
- repeat as necessary

INACTIVE INGREDIENT

Butyrospermum Parkii (Shea) Butter, Cannabis Sativa Hemp Seed Oil and Hemp Derived Cannabidiol (CBD) Extract with proprietary terpene blend (Limonene, Myrcene, Caryophyllene, Linalool, Pinene, Terpineol), Capsicum Frutescens Fruit Extract, Cetearyl Alcohol, Cetearyl Glucoside, Cocos Nucifera (Coconut) Oil, C13-14 Isoparaffin, Deionized Water, Emulsifying Wax, Fragrance, Glyceryl Stearate, Hamamelis Virginiana (Witch Hazel), Laureth-7, Magnesium Chloride, Mangifera Indica (Mango) Seed Butter, Mentha piperita (Peppermint) Leaf Oil, Olea Europaea (Olive) Fruit Oil, Olus Oil (Vegetable), PEG-100 Stearate, Phenoxyethanol, Polyacrylamide, Stearic Acid

Questions

info@ak47painrelief.com